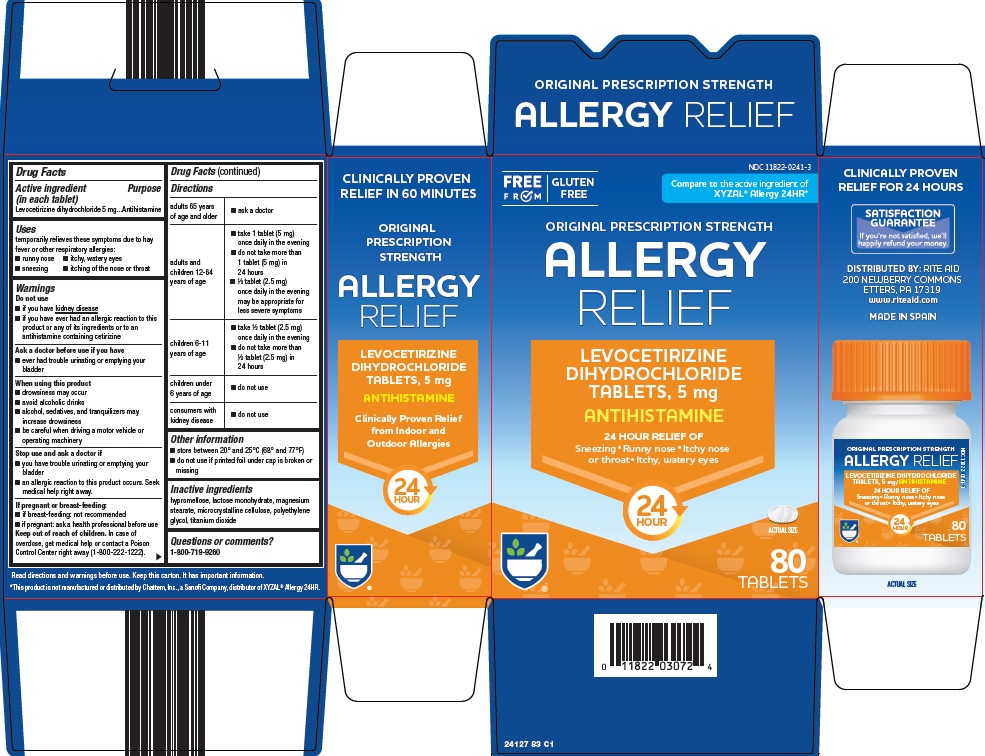 DRUG LABEL: allergy relief
NDC: 11822-0241 | Form: TABLET, FILM COATED
Manufacturer: Rite Aid Corporation
Category: otc | Type: HUMAN OTC DRUG LABEL
Date: 20251009

ACTIVE INGREDIENTS: LEVOCETIRIZINE DIHYDROCHLORIDE 5 mg/1 1
INACTIVE INGREDIENTS: HYPROMELLOSE, UNSPECIFIED; LACTOSE MONOHYDRATE; MAGNESIUM STEARATE; MICROCRYSTALLINE CELLULOSE; POLYETHYLENE GLYCOL, UNSPECIFIED; TITANIUM DIOXIDE

Rite Aid Corporation Allergy Relief Drug Facts

Active ingredient (in each tablet)

Levocetirizine dihydrochloride 5 mg

Purpose

Antihistamine

Uses

temporarily relieves these symptoms due to hay fever or other respiratory allergies:

- runny nose
- itchy, watery eyes
- sneezing
- itching of the nose or throat

Warnings

Do not use

- if you have kidney disease
- if you have ever had an allergic reaction to this product or any of its ingredients or to an antihistamine containing cetirizine

Ask a doctor before use if you have

- ever had trouble urinating or emptying your bladder

When using this product

- drowsiness may occur
- avoid alcoholic drinks
- alcohol, sedatives, and tranquilizers may increase drowsiness
- be careful when driving a motor vehicle or operating machinery

Stop use and ask a doctor if

- you have trouble urinating or emptying your bladder
- an allergic reaction to this product occurs. Seek medical help right away.

If pregnant or breast-feeding:

- if breast-feeding: not recommended
- if pregnant: ask a health professional before use

Keep out of reach of children.

In case of overdose, get medical help or contact a Poison Control Center right away (1-800-222-1222).

Directions

adults 65 years of age and older | - ask a doctor
adults and children 12-64 years of age | - take 1 tablet (5 mg) once daily in the evening - do not take more than 1 tablet (5 mg) in 24 hours - ½ tablet (2.5 mg) once daily in the evening may be appropriate for less severe symptoms
children 6-11 years of age | - take ½ tablet (2.5 mg) once daily in the evening - do not take more than ½ tablet (2.5 mg) in 24 hours
children under 6 years of age | - do not use
consumers with kidney disease | - do not use

Other information

- store between 20° and 25°C (68° and 77°F)
- do not use if printed foil under cap is broken or missing

Inactive ingredients

hypromellose, lactose monohydrate, magnesium stearate, microcrystalline cellulose, polyethylene glycol, titanium dioxide

Questions or comments?

1-800-719-9260

Package/Label Principal Display Panel

FREE FROM | GLUTEN FREE

Compare to the active ingredient of XYZAL® Allergy 24HR

ORIGINAL PRESCRIPTION STRENGTH

ALLERGY RELIEF

LEVOCETIRIZINE DIHYDROCHLORIDE TABLETS, 5 mg

ANTIHISTAMINE

24 HOUR RELIEF OF

Sneezing ● Runny nose ● Itchy nose or throat ● Itchy, watery eyes

24 HOUR

ACTUAL SIZE

80 TABLETS